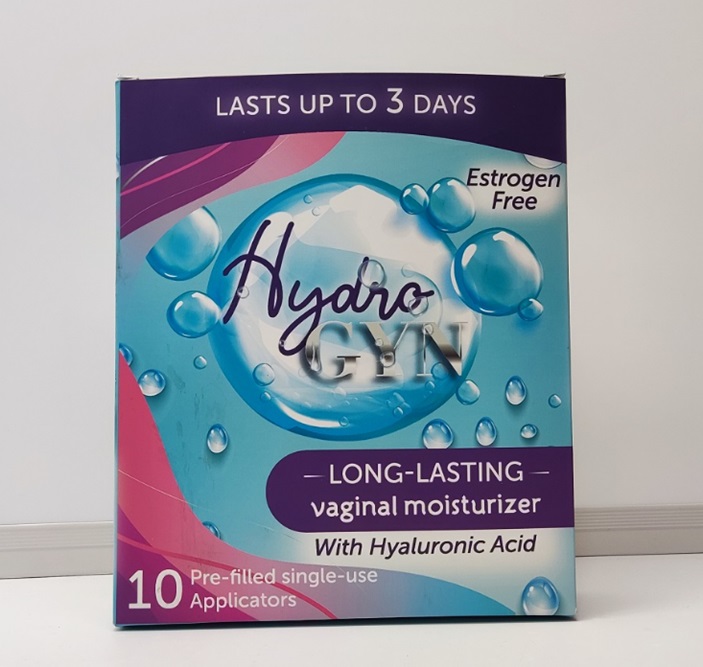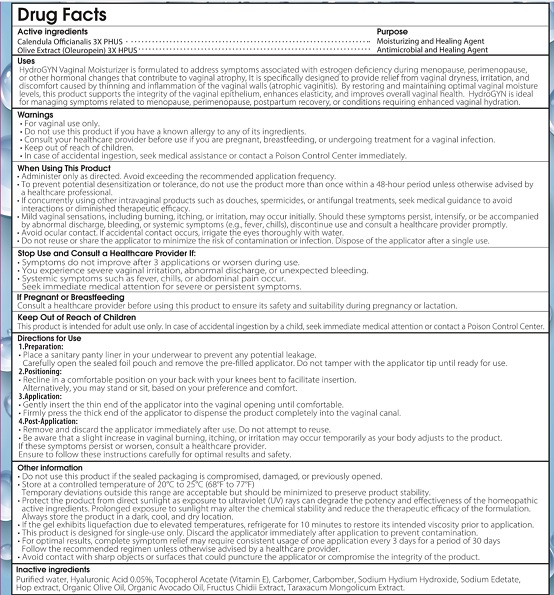 DRUG LABEL: Hydro Gyn
NDC: 85964-001 | Form: GEL
Manufacturer: Shenzhen water element e-commerce Co., LTD
Category: homeopathic | Type: HUMAN OTC DRUG LABEL
Date: 20250808

ACTIVE INGREDIENTS: CALENDULA OFFICINALIS FLOWERING TOP 3 [hp_X]/1 mL; OLEUROPEIN 3 [hp_X]/1 mL
INACTIVE INGREDIENTS: CNIDIUM MONNIERI FRUIT; TARAXACUM MONGOLICUM; HOPS; EDETATE SODIUM; .ALPHA.-TOCOPHEROL ACETATE; AVOCADO OIL; SODIUM HYALURONATE; CARBOMER; SODIUM HYDROXIDE; OLIVE OIL; HYALURONIC ACID; WATER

85964-001-01

Active ingredients

Calendula Offcianalis 3X PHUS
Olive Extract (Oleuropein) 3X HPUS

Purpose

Moisturizing and Healing Agent

Antimicrobial and Healing Agent

Uses

HydroGYN Vaginal Moisturizer is formulated to address symptoms associated with estrogen deficiency during menopause, perimenopause, or other vaginal changes that contribute to vaginal atrophy. It is specifically designed to provide relief from vaginal dryness, irritation, and discomfort caused by thinning and inflammation of the vaginal walls (atrophic vaginitis). By restoring and maintaining optimal vaginal moisture levels, this product helps support the natural vaginal microbiome and may assist in reducing the risk of urinary tract infections associated with vaginal atrophy. It is also suitable for managing symptoms related to menopause, perimenopause, postpartum recovery, or conditions requiring enhanced vaginal hydration.

Warnings

• For vaginal use only.
• Do not use this product if you have a known allergy to any of its ingredients.
• Consult your healthcare provider before use if you are pregnant, breastfeeding, or undergoing treatment for a vaginal infection.
• Do not use this product if the seal is broken or missing.
• In case of accidental ingestion, seek medical assistance or contact a Poison Control Center immediately.

When using this product

• Administer only as directed. Avoid exceeding the recommended application frequency.
• To prevent potential desensitization or tolerance, do not use the product more than once within a 48 - hour period unless otherwise advised by a healthcare professional.
• Before using this product with other therapeutic products such as douches, spermicides, or antifungal treatments, seek medical guidance to avoid interactions or diminished therapeutic efficacy.
• Mild vaginal sensations, including burning, itching, or irritation, may occur initially. Should these symptoms persist, intensify, or be accompanied by abnormal discharge, bleeding, or systemic symptoms (e.g., fever, chills), discontinue use and consult a healthcare provider promptly.
• Do not reuse or share the applicator to minimize the risk of contamination or infection. Dispose of the applicator after a single use.

Stop Use and Consult a Healthcare Provider If

• Symptoms do not improve after 3 applications or worsen during use.
• You experience severe vaginal irritation, abnormal discharge, or unexpected bleeding.
• Systemic symptoms such as fever, chills, or abdominal pain occur.
• Premenopausal women experience any of the above - mentioned symptoms.

If Pregnant or Breastfeeding

Consult a healthcare provider before using this product to ensure its safety and suitability during pregnancy or lactation.

keep out of reach of children

This product is intended for adult use only. In case of accidental ingestion by a child, seek immediate medical attention or contact a Poison Control Center.

Other information

• Do not use this product if the sealed packaging is compromised, damaged, or previously opened.
• Store at a controlled temperature of 20°C to 25°C (68°F to 77°F).
• Protect the product from direct sunlight as excessive ultraviolet (UV) rays may degrade the product stability.
• Temporary deviations outside this range are acceptable but should be minimized to preserve product and effectiveness of the homeopathic ingredients.
• If the product is frozen, thaw it before use.
• Always store the product in a dark, cool, and dry location.

Directions

Preparation:

Place a sanitary panty liner in your underwear to prevent any potential leakage.
Carefully open the sealed foil pouch and remove the pre - filled applicator. Do not tamper with the applicator tip until ready for use.

Positioning:

Recline in a comfortable position on your back with your knees bent to facilitate insertion.
Alternatively, you may stand or sit, based on your preference and comfort.

Application:

Gently insert the thin end of the applicator into the vaginal opening until comfortable.
Firmly press the thick end of the applicator to dispense the product completely into the vaginal canal.

Post - Application:

Remove and discard the applicator immediately after use. Do not attempt to reuse.
Be aware that a slight increase in vaginal burning, itching, or irritation may occur temporarily as your body adjusts to the product.
If these symptoms persist or worsen, consult a healthcare provider.
Ensure to follow these instructions carefully for optimal results and safety.

Inactive ingredients

Purified water, Hyaluronic Acid 0.05%, Tocopherol Acetate (Vitamin E), Carbomer, Carbomer, Sodium Hyaluron Hydroxide, Sodium Edetate, Hop extract, Organic Olive Oil, Organic Avocado Oil, Olive Fruit Vilin Extract, Taraxacum Mongolicum Extract